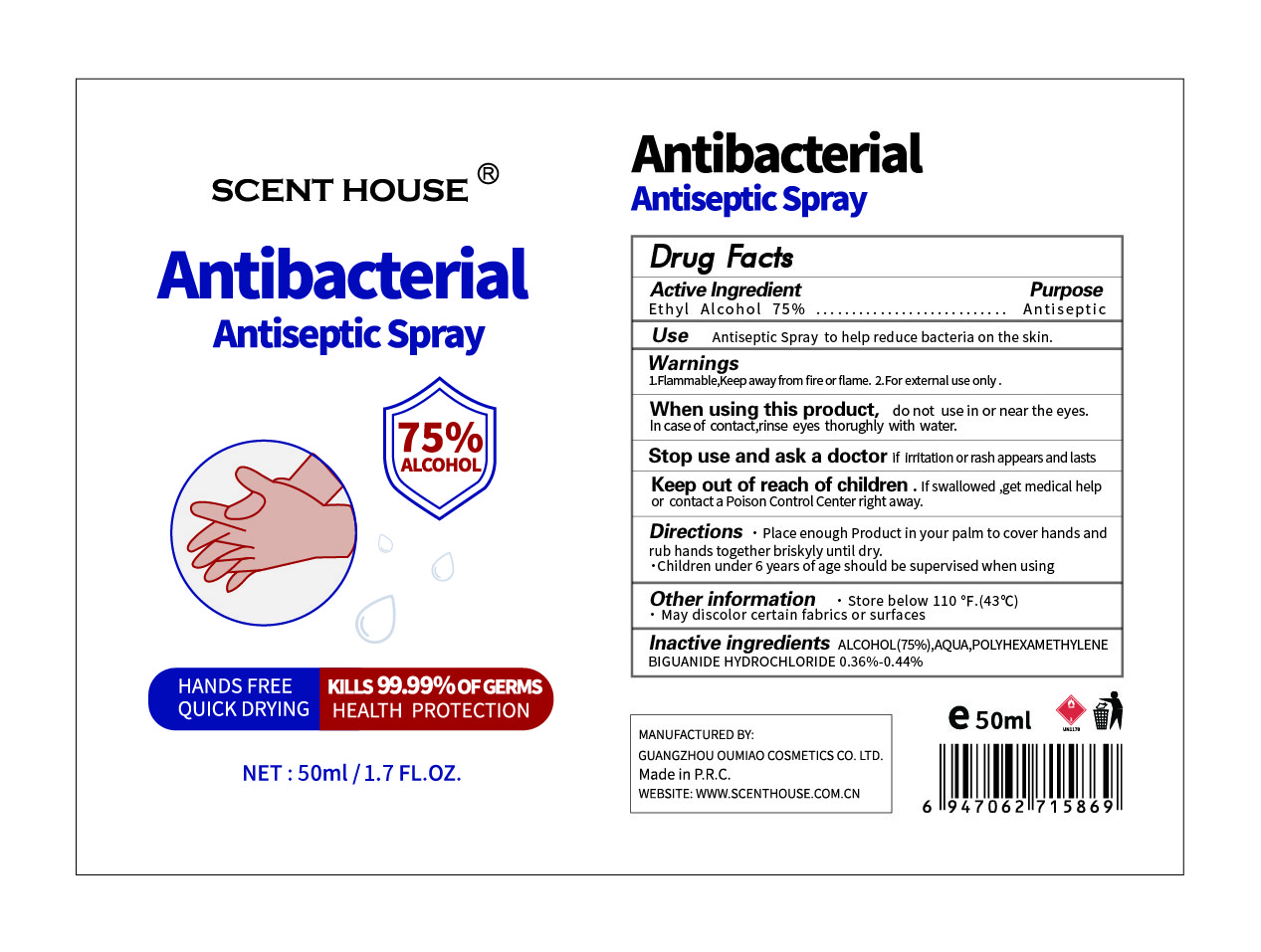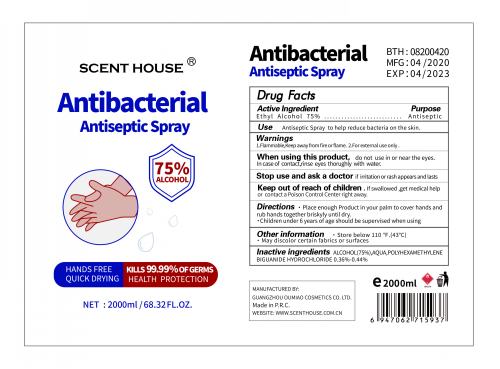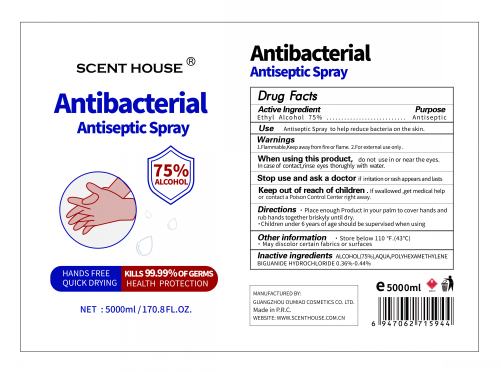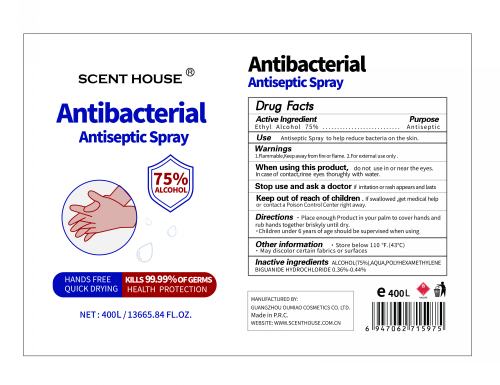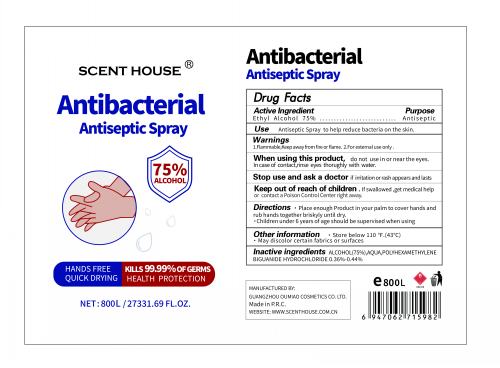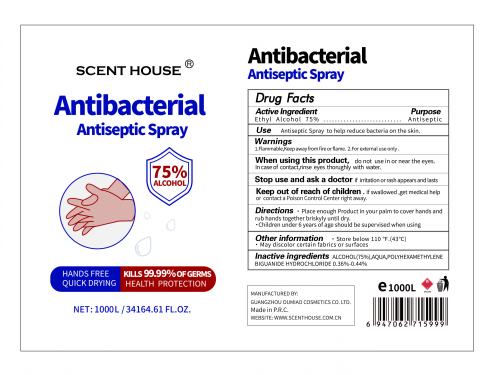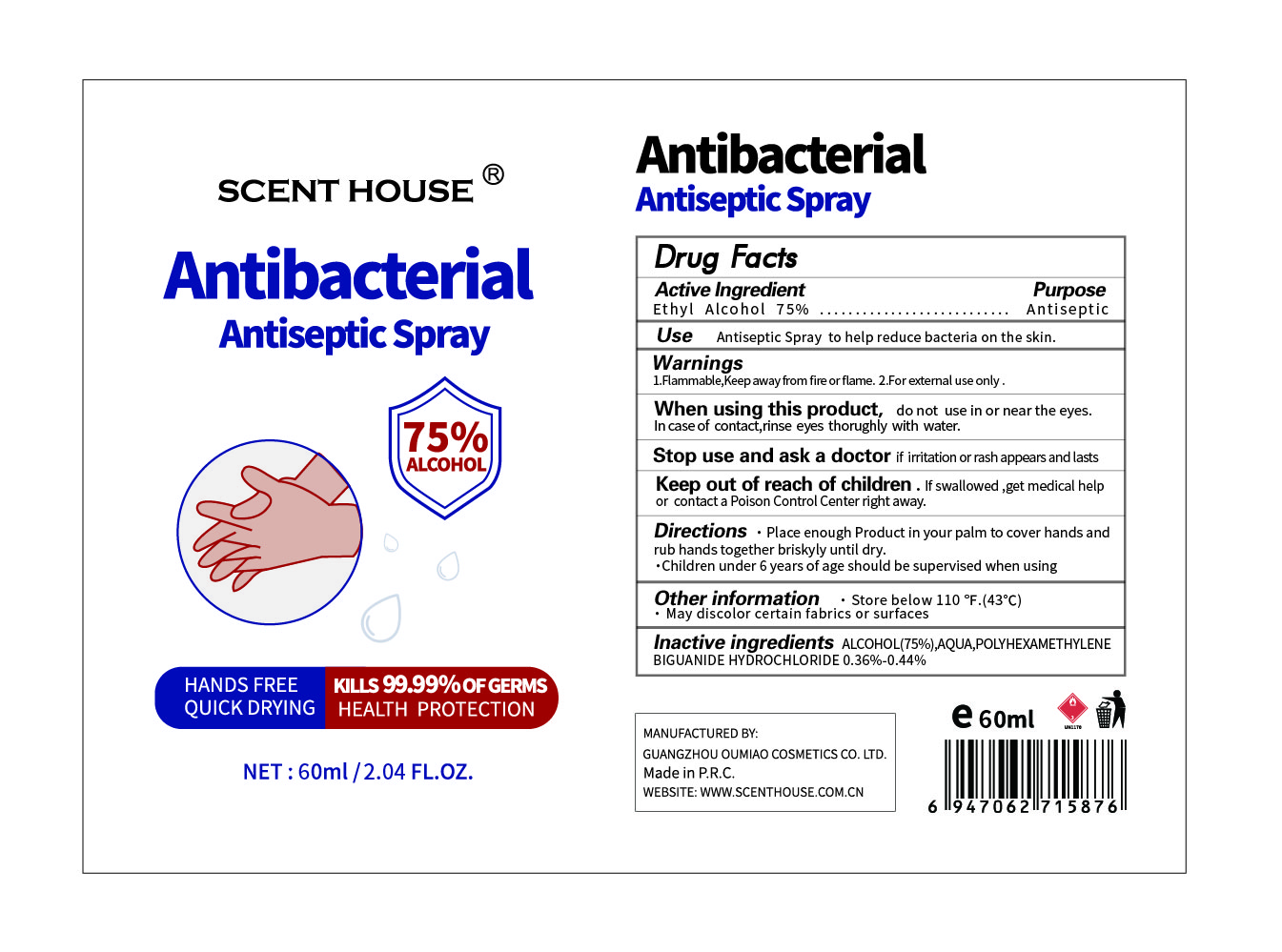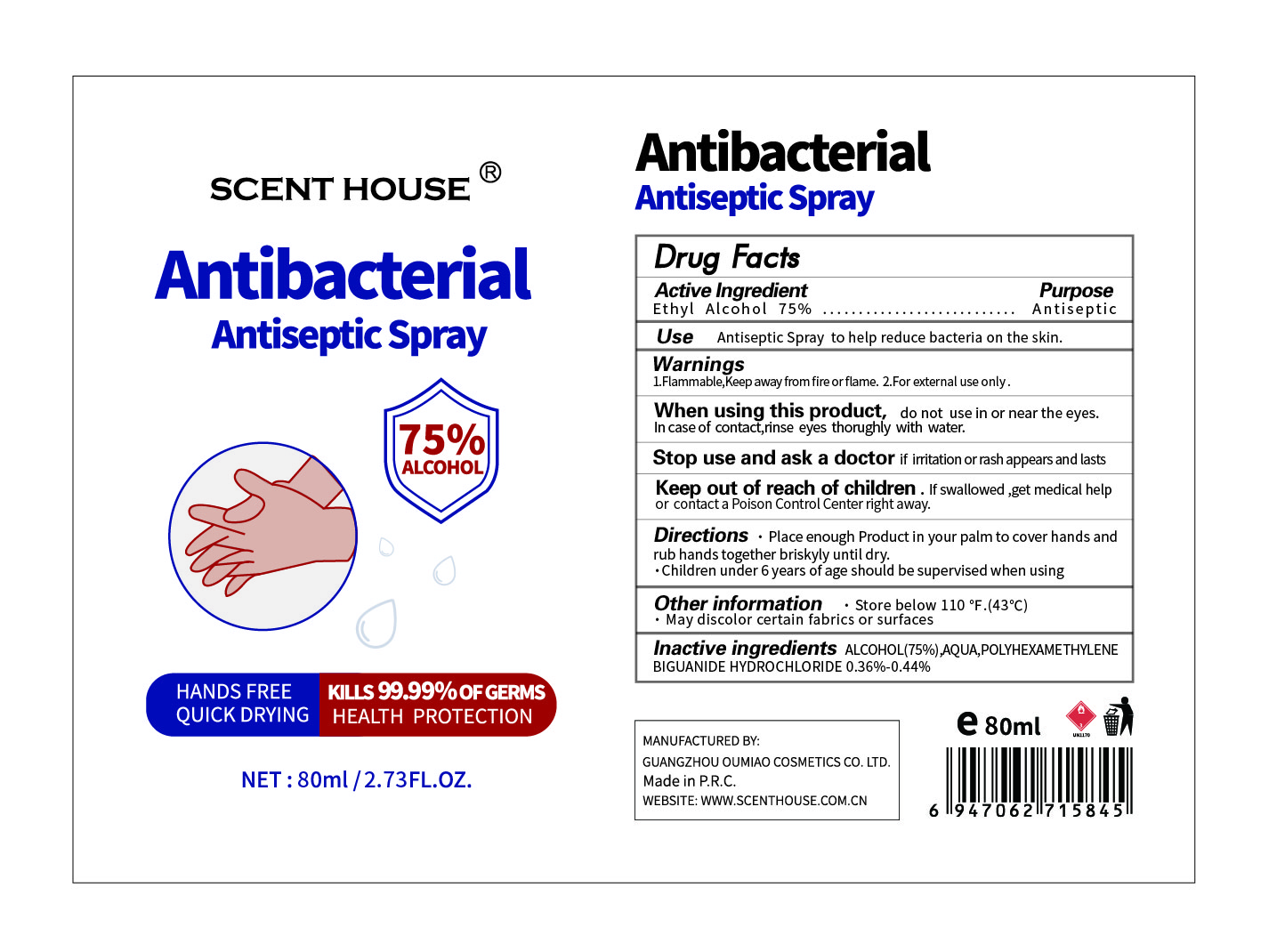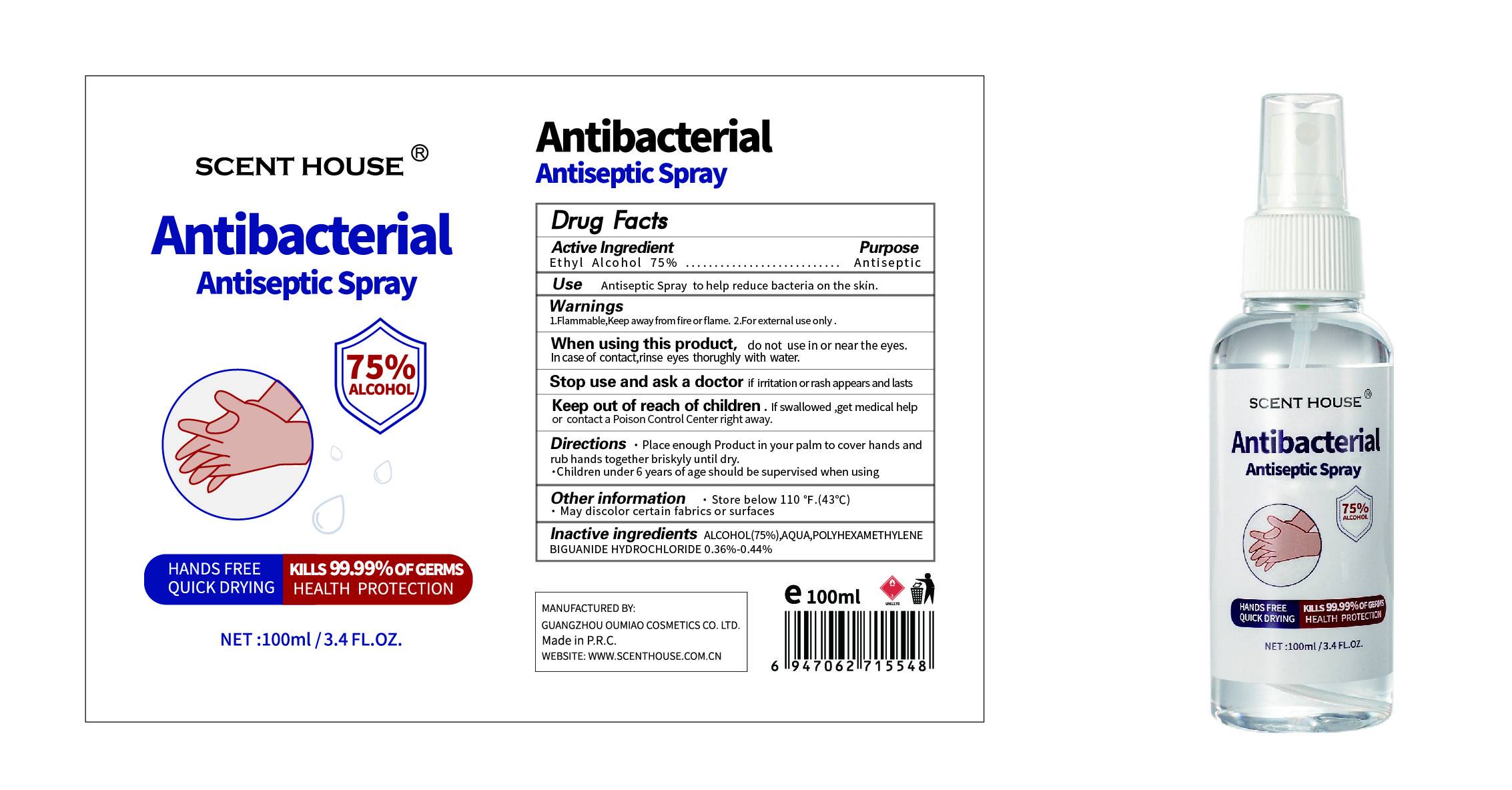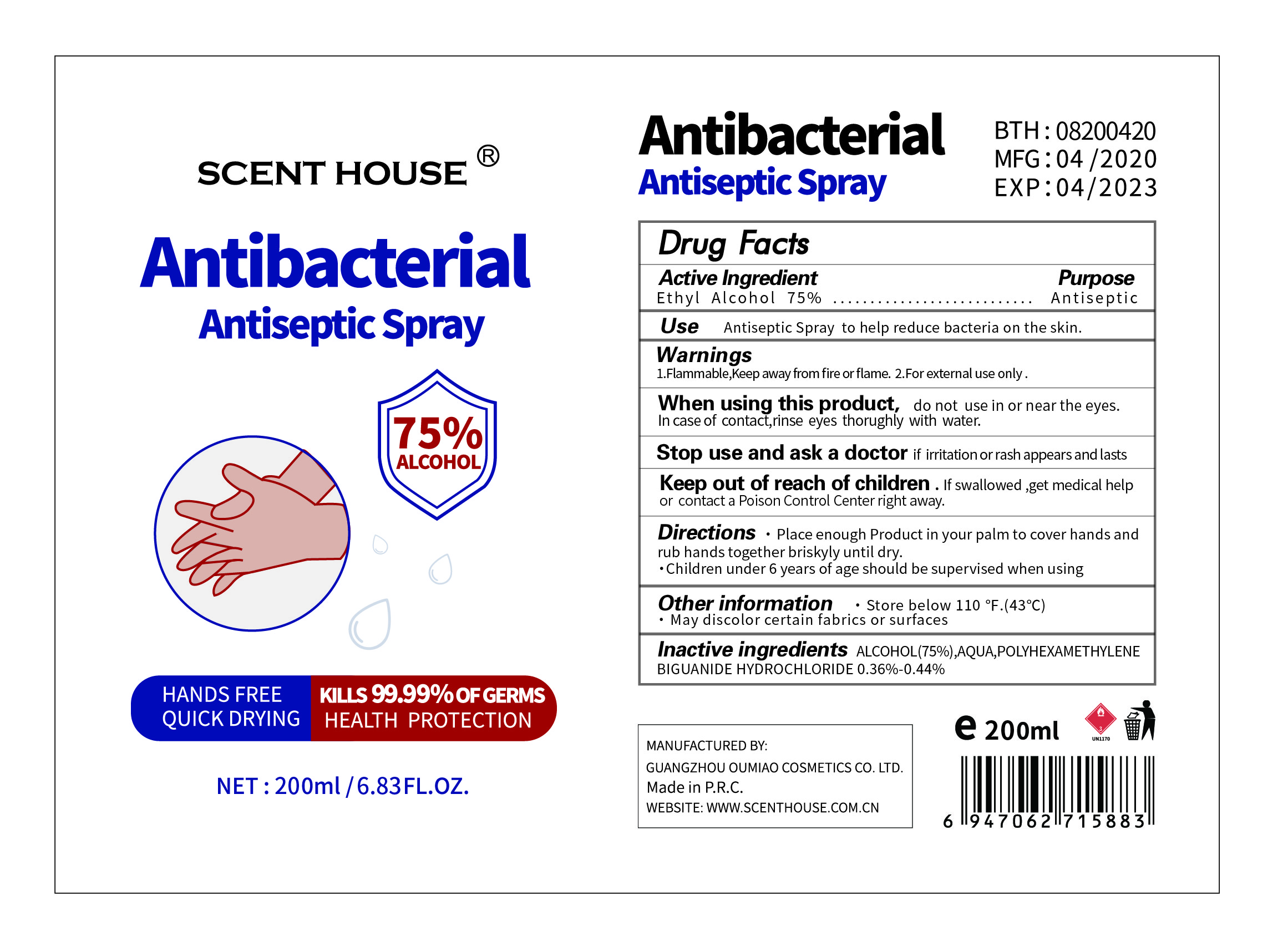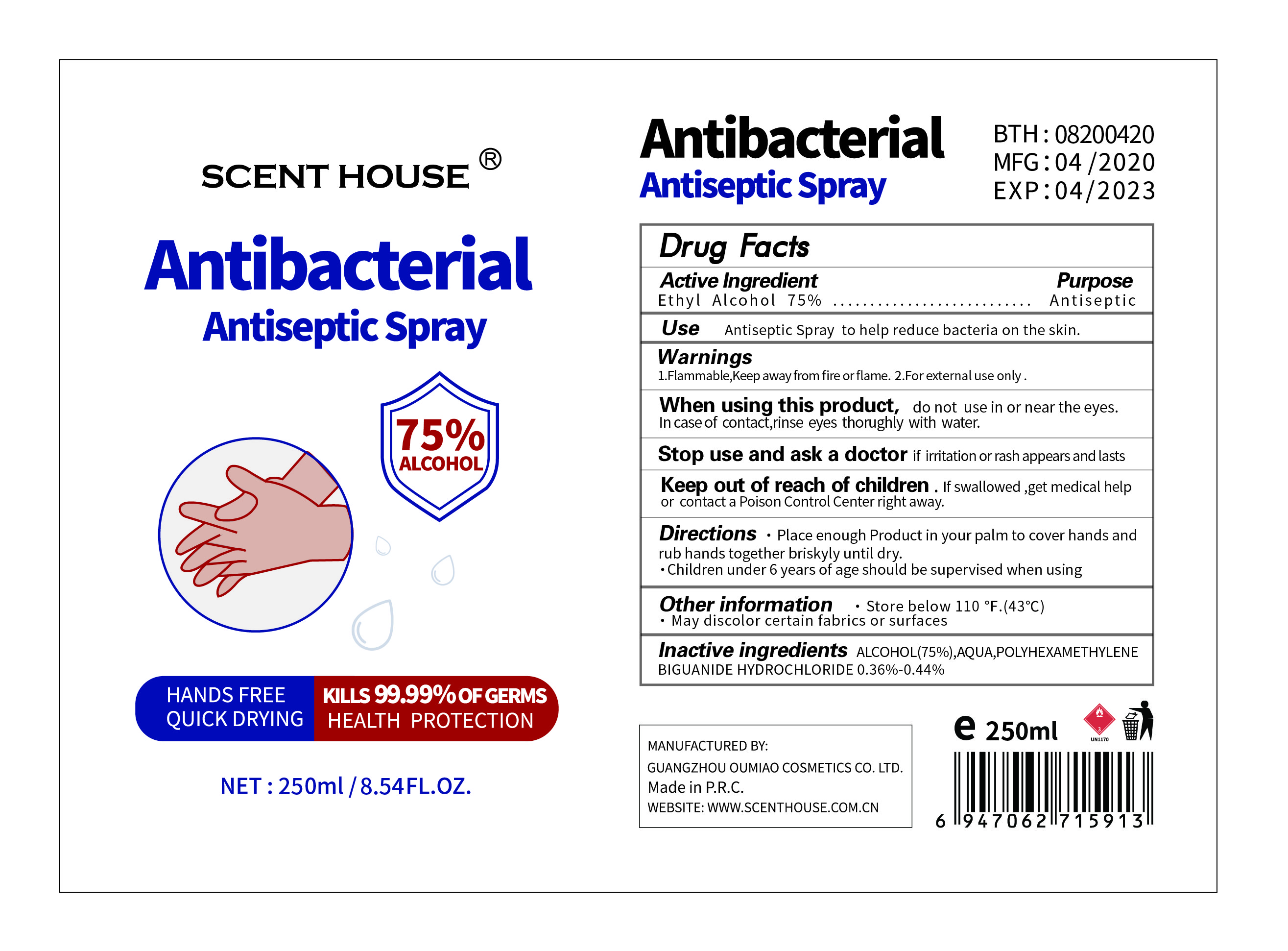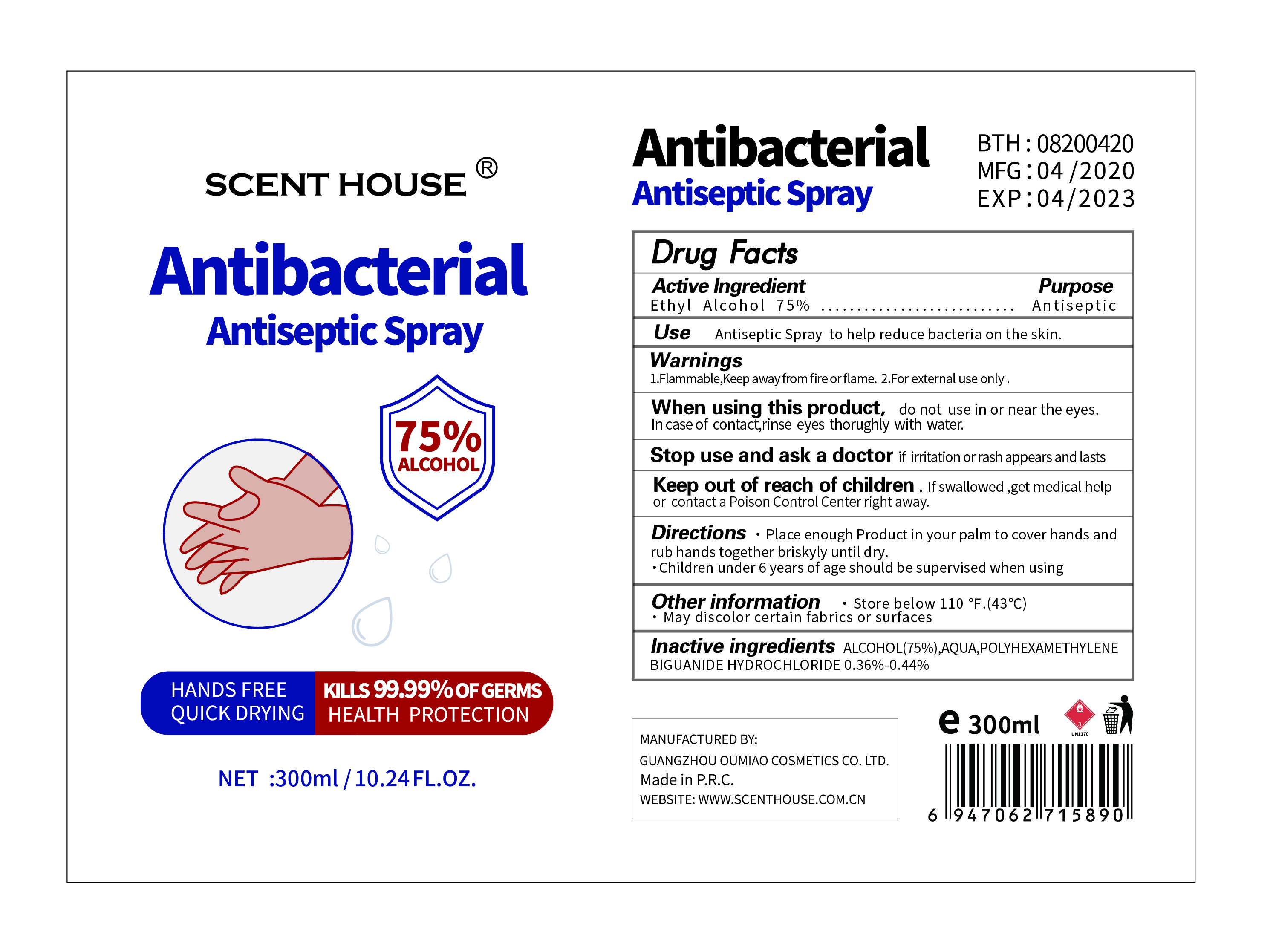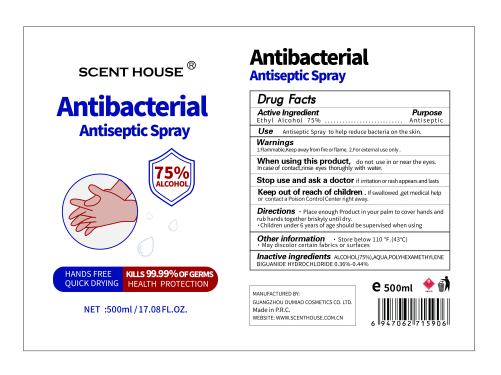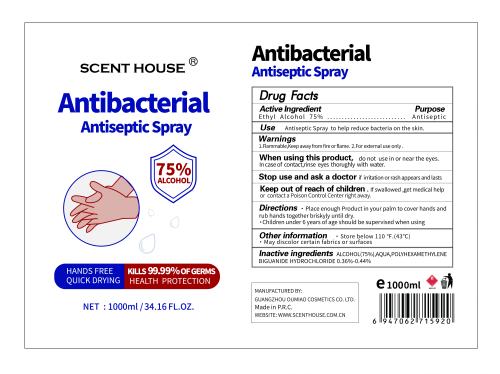 DRUG LABEL: not have
NDC: 74761-002 | Form: SPRAY
Manufacturer: Guangzhou Oumiao Cosmetics Co. Ltd.
Category: otc | Type: HUMAN OTC DRUG LABEL
Date: 20200503

ACTIVE INGREDIENTS: ALCOHOL 75 mL/100 mL
INACTIVE INGREDIENTS: WATER; POLIHEXANIDE HYDROCHLORIDE

Antibacterial Antiseptic Spray

Active Ingredient

Ethyl Alcohol 75%

Purpose

Antiseptic

Use

Antiseptic Spray to help reduce bacteria on the skin.

Warnings

1.Flammable,Keep away from fire or flame.

2.For external use only.

When using this product

do not use in or near the eyes. In case of contact,rinse eyes thorughly with water.

Stop use and ask a doctor if irritation or rash appears and lasts

Keep out of reach of children

If swallowed, get medical help or contact a Poison Control Center right away.

Directions

Place enough Product in your palm to cover hands and rub hands together briskyly until dry.

Children under 6 years of age should be supervised when using

Other information

Store below 110°F.(43℃)·

May discolor certain fabrics or surfaces.

Inactive ingredients

ALCOHOL(75%) , AQUA, POLYHEXAMETHYLENE BIGUANIDE HYDROCHLORIDE 0.36%-0.44%